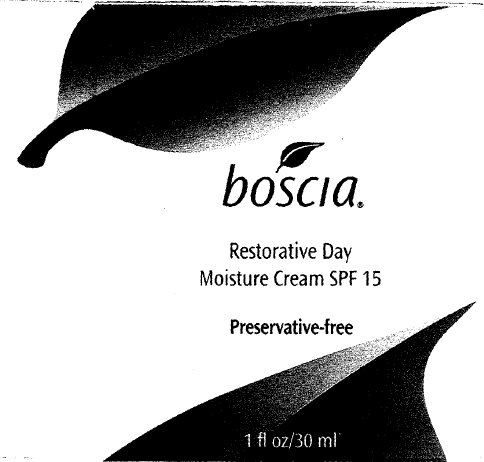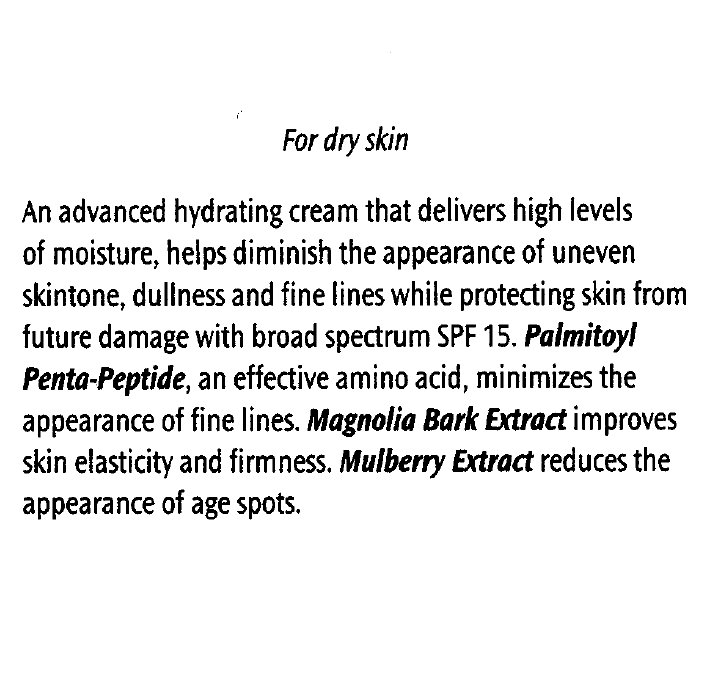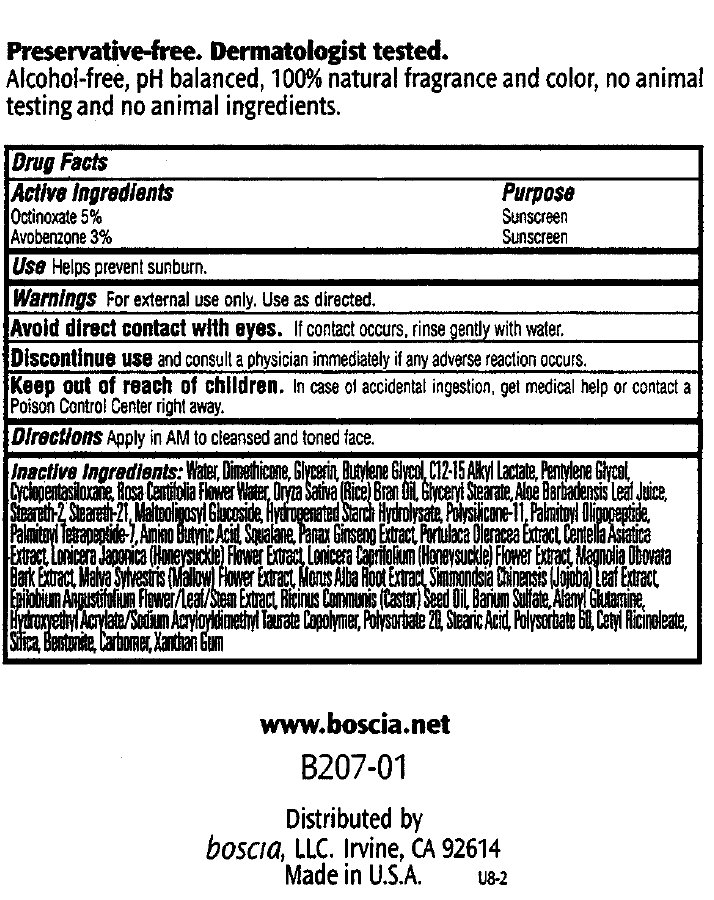 DRUG LABEL: Restorative Day Moisture SPF 15
NDC: 76151-207 | Form: CREAM
Manufacturer: Boscia LLC
Category: otc | Type: HUMAN OTC DRUG LABEL
Date: 20231212

ACTIVE INGREDIENTS: OCTINOXATE 50 mg/1 mL; AVOBENZONE 30 mg/1 mL
INACTIVE INGREDIENTS: MORUS ALBA ROOT; EPILOBIUM ANGUSTIFOLIUM FLOWERING TOP; CASTOR OIL; BARIUM SULFATE; ALANYL GLUTAMINE; POLYSORBATE 20; STEARIC ACID; POLYSORBATE 60; SILICON DIOXIDE; BENTONITE; XANTHAN GUM; BUTYLENE GLYCOL; WATER; DIMETHICONE; GLYCERIN; PENTYLENE GLYCOL; CYCLOMETHICONE 5; ROSA CENTIFOLIA FLOWER OIL; RICE BRAN OIL; GLYCERYL MONOSTEARATE; ALOE VERA LEAF; STEARETH-2; STEARETH-21; PALMITOYL OLIGOPEPTIDE; PALMITOYL TETRAPEPTIDE-7; SQUALANE; PANAX GINSENG FLOWER; CENTELLA ASIATICA; LONICERA JAPONICA FLOWER; MAGNOLIA OBOVATA BARK; MALVA SYLVESTRIS FLOWER

Restorative Day Moisture Cream SPF 15

ACTIVE INGREDIENT

Active Ingredients Purpose Octinoxate 5% Sunscreen Avobenzone 3% Sunscreen

PURPOSE

Use Helps prevent sunburn.

Use

Helps prevent sunburn.

Warnings For external use only. Use as directed.

WHEN USING

Avoid direct contact with eyes. If contact occurs, rinse gently with water.

STOP USE

Discontinue use and consult a physician immediately if any adverse reaction occurs.

Keep out of reach of children.

OTHER SAFETY INFORMATION

In case of accidental ingestion, get medical help or contact a Poison Control Center right away.

DOSAGE AND ADMINISTRATION

Directions Apply in AM to cleansed and toned face.

INACTIVE INGREDIENT

Inactive Ingredients: Water, Dimethicone, Glycerin, Butylene Glycol, C12-15 Alkyl Lactate, Pentylene Glycol, Cyclopentasiloxane, Rosa Centifolia Flower Water, Oryza Sativa (Rice) Bran Oil, Glyceryl Stearate, Aloe Barbadensis Leaf Juice, Steareth-2, Steareth-21, Maltooligosyl Glucoside, Hydrogenated Starch Hydrolysate, Polysilicone-11, Palmitoyl Oligopeptide, Palmitoyl Tetrapeptide-7, Amino Butyric Acid, Squalane, Panax Ginseng Extract, Portulace Oleracea Extract, Centella Asiatica Extract, Lonicera Japonica (Honeysuckle) Flower Extract, Lenicera Caprifolium (Honeysuckle) Flower Extract, Magnolia Obovata Bark Extract, Malva Sylvestris (Mallow) Flower Extract, Morus Alba Root Extract, Simmondsia Chinensis (Jojoba) Leaf Extract, Epilobium Angustifolium Flower/Leaf/Stem Extract, Ricinus Communis (Castor) Seed Oil, Barium Sulfate, Alanyl Glutamine, Hydroxyethyl Acrylate/Sodium Acryloyldimethyl Taurate Copolymer, Polysorbate 20, Stearic Acid, Polysorbate 60, Cetyl Ricinoleate, Silica, Bentonite, Carbomer, Xanthan Gum.

DESCRIPTION

Preservative-free. Dermatologist tested. Alcohol-free, pH balanced, 100% natural fragrance and color, no animal testing and no animal ingredients. www.boscia.net B207-01 Distributed by boscia, LLC. Irvine, CA 92614 Made in U.S.A. U8-2

PACKAGE LABEL

For dry skin An advanced hydrating cream that delivers high levels of moisture, helps diminish the appearance of uneven skintone, dullness and fine lines while protecting skin from future damage with broad spectrum SPF 15. Palmitoyl Penta-Peptide, an effective amino acid, minimizes the appearance of fine lines. Magnolia Bark Extract improves skin elasticity and firmness. Mulberry Extract reducess the appearance of age spots.

PACKAGE LABEL

boscia Restorative Day Moisture Cream SPF 15 Preservative-free 1 fl oz/30 ml

PACKAGE LABEL

www.boscia.net B207-01 Distributed by boscia, LLC. Irvine, CA 92614 Made in U.S.A. U8-2